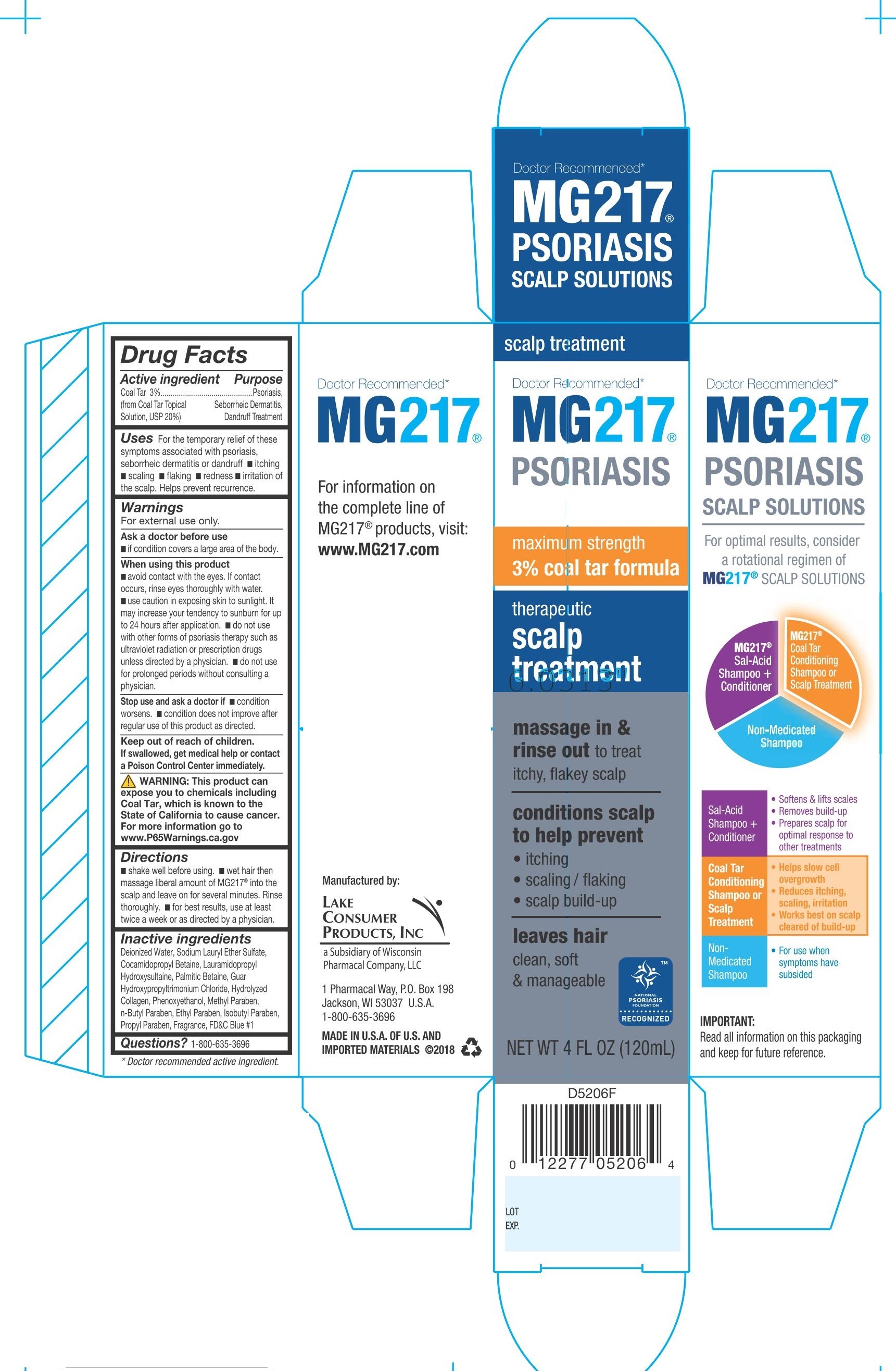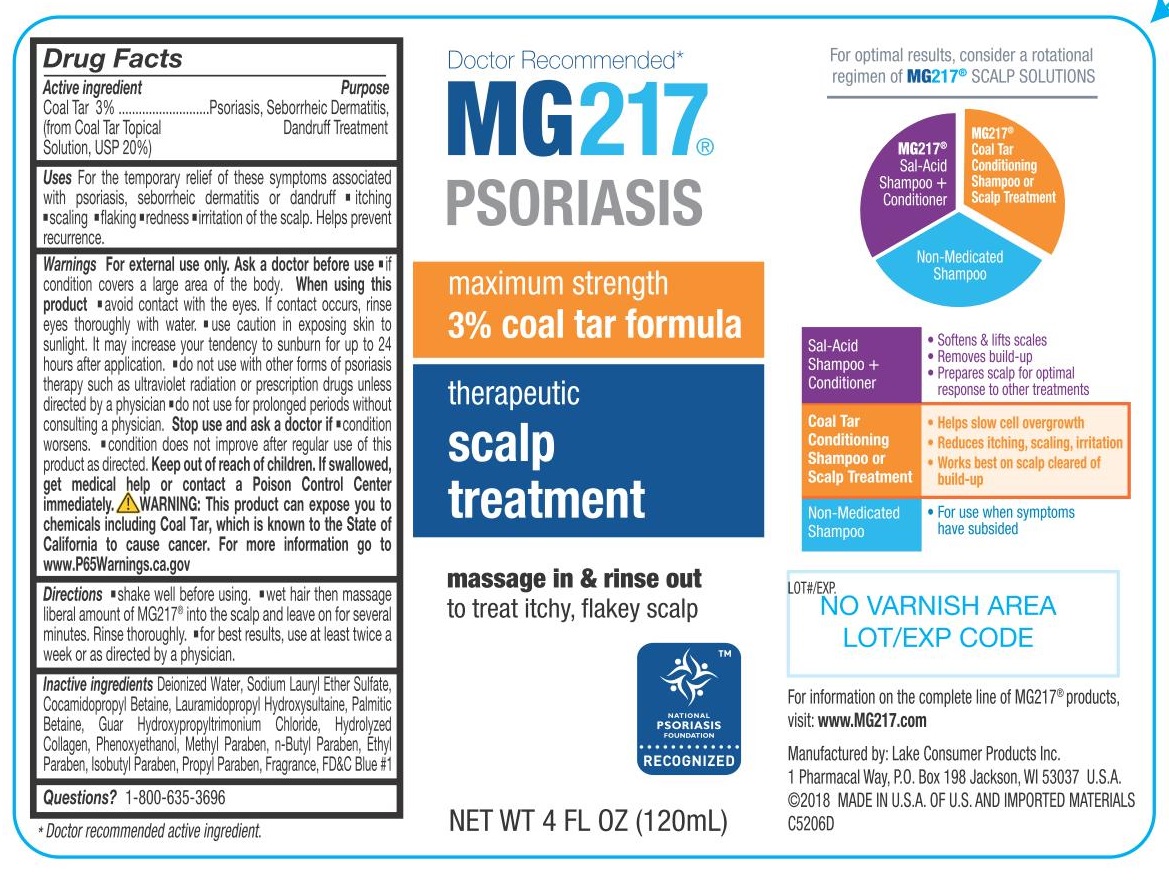 DRUG LABEL: MG217 Psoriasis
NDC: 68093-5206 | Form: SHAMPOO
Manufacturer: Wisconsin Pharmacal Company
Category: otc | Type: HUMAN OTC DRUG LABEL
Date: 20181210

ACTIVE INGREDIENTS: COAL TAR 0.03 g/1 g
INACTIVE INGREDIENTS: WATER; SODIUM LAURETH SULFATE; COCAMIDOPROPYL BETAINE; LAURAMIDOPROPYL HYDROXYSULTAINE; PHENOXYETHANOL; CETYL BETAINE; GUAR GUM; PORK COLLAGEN; METHYLPARABEN; BUTYLPARABEN; ISOBUTYLPARABEN; PROPYLPARABEN; FD&C BLUE NO. 1; ETHYLPARABEN

Drug Facts

Active Ingredient

Coal Tar 3%

(from Coal Tar Topical Solution, USP 20%)

Purpose

Psoriasis, Seborrheic Dermatitis, Dandruff Treatment

INDICATIONS AND USAGE

Uses For the temporary relief of these symptoms associated with psoriasis, seborrheic dermatitis or dandruff

- itching
- scaling
- flaking
- redness
- irritation ofthe scalp.

Helps prevent recurrence.

Warnings

For external use only.

Ask doctor before use

if condition covers a large area of the body.

When using this product

- avoid contact with the eyes. If contact occurs, rinse eyes thoroughly with water.
- use caution in exposing skin to sunlight. It may increase your tendency to sunburn for up to 24 hours after application.
- do not use with other forms of psoriasis therapy such as ultraviolet radiation or prescription drugs unless directed by a physician.
- do not use for prolonged periods without consulting a physician.

Stop use and ask a doctor if

- condition worsens.
- condition does not improve after regular use of this product as directed.

Keep out of reach of children.

If swallowed, get medical help or contact a Poison Control Center immediately.

OTHER SAFETY INFORMATION

WARNING This product can gose you to chemicals including Coal Tar, which is known to the State of California to cause cancer.
For more information go to www.P65Warnings.ca.gov

Directions

- shake well before using.
- wet hair then massage liberal amount of MG217 into the scalp and leave on for several minutes. Rinse thoroughly.
- for best results, use at least twice a week or as directed by a physician.

Inactive ingredients

Deionized water, Sodium Alkyl Ether Sulfate, Cocamidopropyl Betaine, Lauramidopropyl Hydroxysultaine, Palmitic Betaine, Guar Hydroxypropyltrimonium Chloride, Hydrolyzed Collagen, Phenoxyethanol, Methyl Paraben, n-Butyl Paraben, Ethyl Paraben, Isobutyl Paraben, Propyl Paraben, Fragrance FD and C No. 1

Questions?

1-800-635-3696